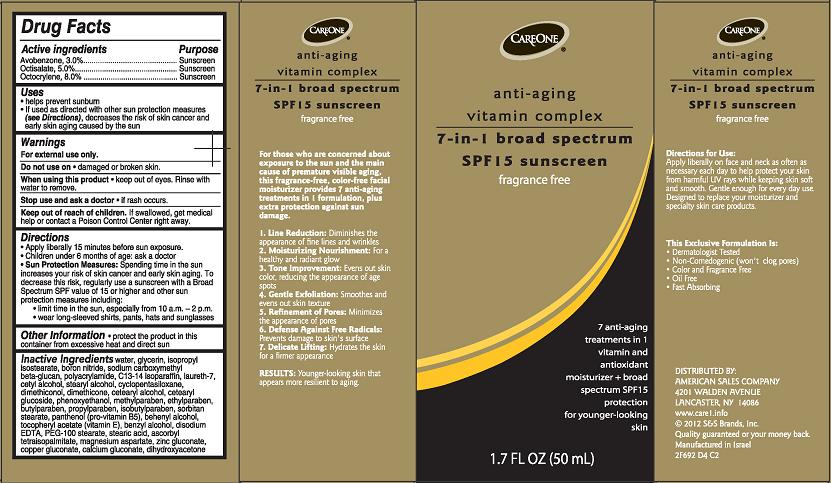 DRUG LABEL: Anti-Aging Vitamin Complex 7-in-1 Broad Spectrum SPF15 Sunscreen
NDC: 41520-693 | Form: CREAM
Manufacturer: American Sales Company
Category: otc | Type: HUMAN OTC DRUG LABEL
Date: 20130927

ACTIVE INGREDIENTS: AVOBENZONE 3 g/100 mL; OCTISALATE 5 g/100 mL; OCTOCRYLENE 8 g/100 mL
INACTIVE INGREDIENTS: WATER; GLYCERIN; ISOPROPYL ISOSTEARATE; BORON NITRIDE; CARBOXYMETHYLCELLULOSE SODIUM; POLYACRYLAMIDE (10000 MW); C13-14 ISOPARAFFIN; LAURETH-7; CETYL ALCOHOL; STEARYL ALCOHOL; CYCLOMETHICONE 5; DIMETHICONOL (100000 CST); DIMETHICONE; CETOSTEARYL ALCOHOL; CETEARYL GLUCOSIDE; PHENOXYETHANOL; METHYLPARABEN; ETHYLPARABEN; BUTYLPARABEN; PROPYLPARABEN; ISOBUTYLPARABEN; SORBITAN MONOSTEARATE; PANTHENOL; DOCOSANOL; .ALPHA.-TOCOPHEROL ACETATE; BENZYL ALCOHOL; EDETATE DISODIUM; PEG-100 STEARATE; STEARIC ACID; ASCORBYL TETRAISOPALMITATE; MAGNESIUM ASPARTATE; ZINC GLUCONATE; COPPER GLUCONATE; CALCIUM GLUCONATE; DIHYDROXYACETONE

CareOne anti-aging vitamin complex 7-in-1 broad spectrum SPF15 sunscreen

Active ingredient

Avobenzone 3.0%

Octisalate 5.0%

Octocrylene 8.0%

Purpose

Sunscreen

Uses

- helps prevent sunburn
- If used as directed with other sun protection measures (see Directions), decreases the risk of skin cancer and early skin aging caused by the sun

Warnings

For external use only.

Do not use on

- damaged or broken skin.

When using this product

- keep out of eyes. Rinse with water to remove.

Stop use and ask a doctor

- if rash occurs.

Keep Out of Reach of Children

If swallowed, get medical help or contact a Poison Control Center right away.

Directions

- Apply liberally 15 minutes before sun exposure.
- Children under 6 months: ask a doctor.
- Sun Protection Measures: Spending time in the sun increases your risk of skin cancer and early skin aging. To decrease this risk regularly use a sunscreen with a Broad Spectrum SPF value of 15 or higher and other sun protection measures including:
  - limit time in the sun, especially from 10 a.m. - 2 p.m.
  - wear long-sleeved shirts, pants, hats and sunglasses.

Other Information

- protect the product in this container from excessive heat and direct sun

Inactive Ingredients

water, glycerin, isopropyl isostearate, boron nitride, sodium carboxymethyl beta-glucan, polyacrylamide, C13-14 isoparaffin, laureth-7, cetyl alcohol, stearyl alcohol, cyclopentasiloxane, dimethiconol, dimethicone, cetearyl alcohol, cetearyl glucoside, phenoxyethanol, methylparaben, ethylparaben, butylparaben, propylparaben, isobutylparaben, sorbitan stearate, panthenol (pro-vitamin B5), behenyl alcohol, tocopheryl acetate (vitamin E), benzyl alcohol, disodium EDTA, PEG-100 stearate, stearic acid, ascorbyl tetraisopalmitate, magnesium aspartate, zinc gluconate, copper gluconate, calcium gluconate, dihydroxyacetone

Package/Label Principal Display Panel

CAREONE® anti-aging vitamin complex
7-in-1 broad spectrum
SPF 15 sunscreen
fragrance free

7 anti-aging treatments in 1 vitamin and antioxidant moisturizer + broad spectrum SPF15 protection for younger-looking skin

1.7 FL OZ (50 mL)

For those who are concerned about exposure to the sun and the main cause of premature visible aging, this fragrance-free, color-free facial moisturizer provides 7 anti-aging treatments in 1 formulation, plus extra protection against sun damage.

1. Line Reduction: Diminishes the appearance of fine lines and wrinkles
2. Moisturizing Nourishment: for a healthy and radiant glow
3. Tone Improvement: Evens out skin color, reducing the appearance of age spots
4. Gentle Exfoliation: Smoothes and evens out skin texture
5. Refinement of Pores: Minimizes the appearance of pores
6. Defense Against Free Radicals: Prevents damage to skin's surface
7. Delicate Lifting: Hydrates the skin for a firmer appearance

RESULTS: Younger-looking skin that appears more resilient to aging.

Directions for Uses:
Apply liberally on face and neck as often as necessary each day to help protect your skin from harmful UV rays while keeping skin soft and smooth. Gentle enough for every day use. Designed to replace your moisturizer and specially skin care products.

This Exclusive Formulation Is:

- Dermatologist Tested
- Non-Comedogenic (won't clog pores)
- Color and Fragrance Free
- Oil Free
- Fast Absorbing

DISTRIBUTED BY:

AMERICAN SALES COMPANY
4201 WALDEN AVENUE
LANCASTER, NY 14086
www.care1.info
© 2012 S&S Brands, Inc
Quality guaranteed or your money back.
Manufactured in Israel

2F692 D4 C2

Carton Label